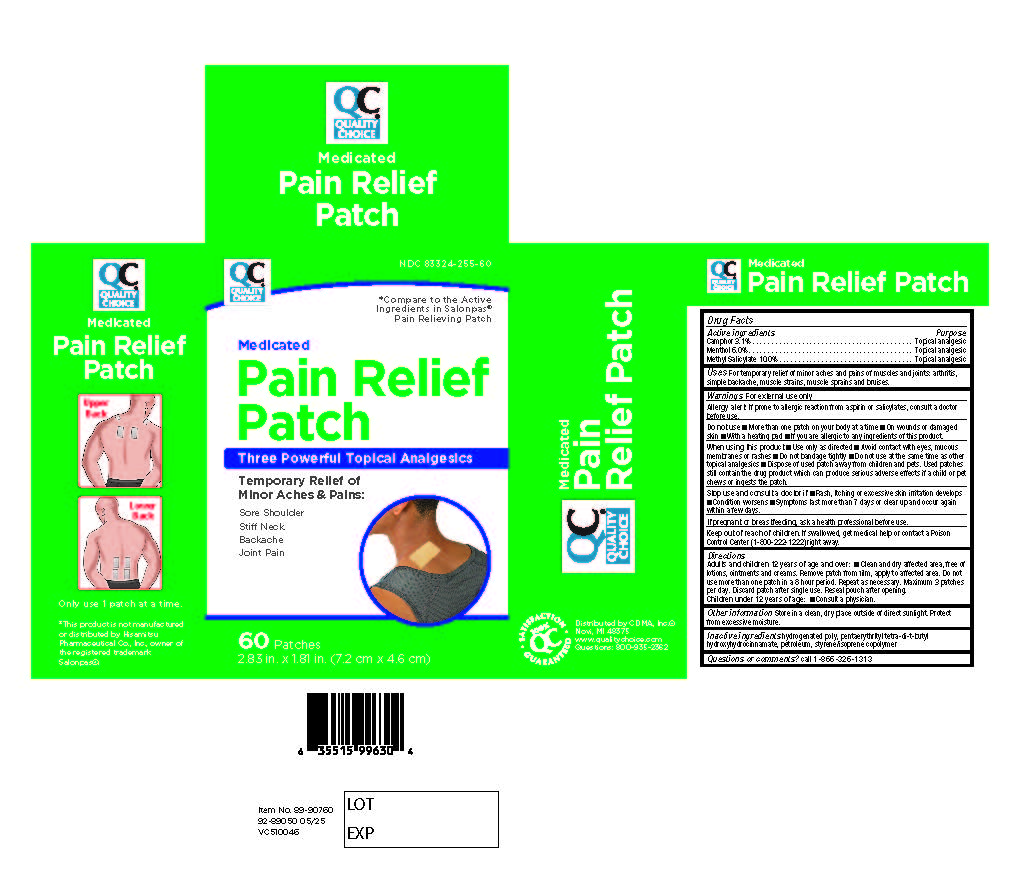 DRUG LABEL: Pain Relief Patch
NDC: 83324-255 | Form: PATCH
Manufacturer: CDMA, Inc.
Category: otc | Type: HUMAN OTC DRUG LABEL
Date: 20250709

ACTIVE INGREDIENTS: CAMPHOR (SYNTHETIC) 3.1 g/1 1; MENTHOL 6 g/1 1; METHYL SALICYLATE 10 g/1 1
INACTIVE INGREDIENTS: HYDROGENATED C6-20 POLYOLEFIN (100 CST); PENTAERYTHRITOL TETRAKIS(3-(3,5-DI-TERT-BUTYL-4-HYDROXYPHENYL)PROPIONATE); LIQUID PETROLEUM; STYRENE/ISOPRENE COPOLYMER (28:72; 210000 MW)

Pain Relief Patch

Active Ingredients

Camphor 3.1% - Topical analgesic

Menthol 6.0% - Topical analgesic

Methyl Salicylate 10.0% - Topical analgesic

Purpose

Topical analgesic

Uses

Temporary relief of minor aches and pains of muscles and joints: arthritis, simple backache, muscle strains, muscle sprains, and bruises.

Warnings

For external use only.

Allergy alert: If prone to allergic reaction from aspirin or salicylates, consult a doctor before use.

Directions

Adults and children 12 years of age and over: Clean and dry affected area, free of lotions, ointments and creams. Remove patch from film, apply to affected area. Do not use more than one patch in an 8 hour period. Repeat as necessary. Maximum 3 patches per day. Discard patch after single use. Reseal pouch after opening.

Children under 12 years of age: Consult a physician.

Other Information

Store in a clean, dry place outside of direct sunlight. Protect from excessive moisture.

Inactive Ingredients

Hydrogenated poly

Pentaerythrityl tetra-di-t-butyl hydroxyhydrocinnamate

Petroleum

Styrene/isoprene copolymer

Keep out of reach of children. If swallowed, get medical help or contact a Poison Control Center (1-800-222-1222) right away.

PREGNANCY OR BREAST FEEDING

If pregnant or breastfeeding, ask a health professional before use.

Stop use and consult a doctor if rash, itching or excessive skin irritation develops, condition worsens, symptoms last more than 7 days or clear up and occur again within a few days.

Do not use more than one patch on your body at a time, on wounds or damaged skin, with a heating pad, or if you are allergic to any ingredients of this product.

When using this product: Use only as directed, avoid contact with eyes, mucous membranes or rashes, do not bandage tightly, do not use at the same time as other topical analgesics.